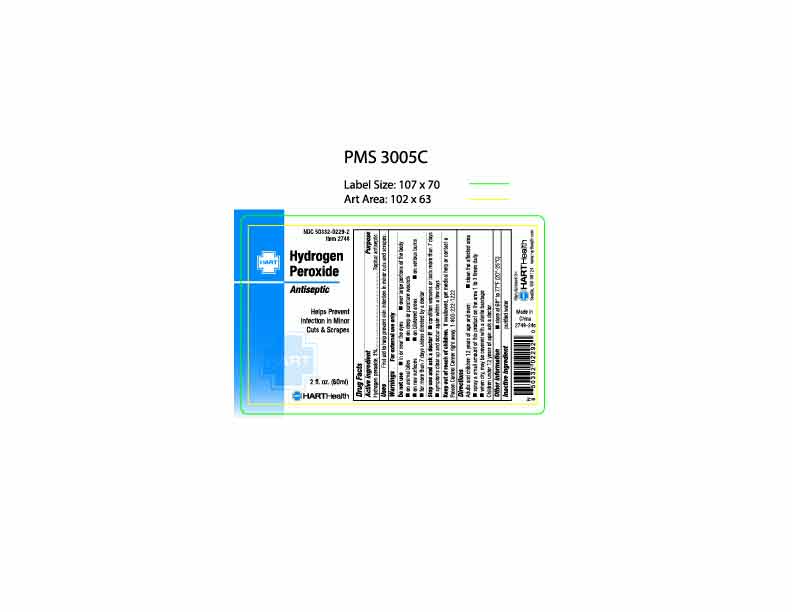 DRUG LABEL: Hydrogen Peroxide
NDC: 50332-0229 | Form: SPRAY
Manufacturer: HART Health
Category: otc | Type: HUMAN OTC DRUG LABEL
Date: 20250610

ACTIVE INGREDIENTS: hydrogen peroxide 30 mg/1 mL
INACTIVE INGREDIENTS: WATER

Hydrogen Peroxide Spray

Active Ingredient

Hydrogen Peroxide 3.0%

Purpose

Topical Antiseptic

Uses

First aid to help prevent skin infection in minor cuts and scrapes

Warnings

For external use only.

Do not use

- in or near the eyes
- over large portions of the body
- on animal bites
- on deep or puncture wounds
- on raw surfaces
- on blistered areas
- on serious burns
- for more than 7 days unless directed by a doctor

Stop use and ask a doctor if

- condition worsens or lasts more than 7 days
- symptoms clear up and occur again within a few days

Keep out of reach of children.

If swallowed, get medicla help or contact a Poison Control Center right away. 1-800-222-1222

Directions:

Adults and children 12 years of age and over:

- clean the affected area
- spray a small amount of this product on the area 1 to3 times daily
- when dry, may be covered with a sterile bandage

Childred under 12 year of age: ask a doctor

Other information

sotre at 68° to 77°F (20° to 25°C)

Inactive ingredient

purified water